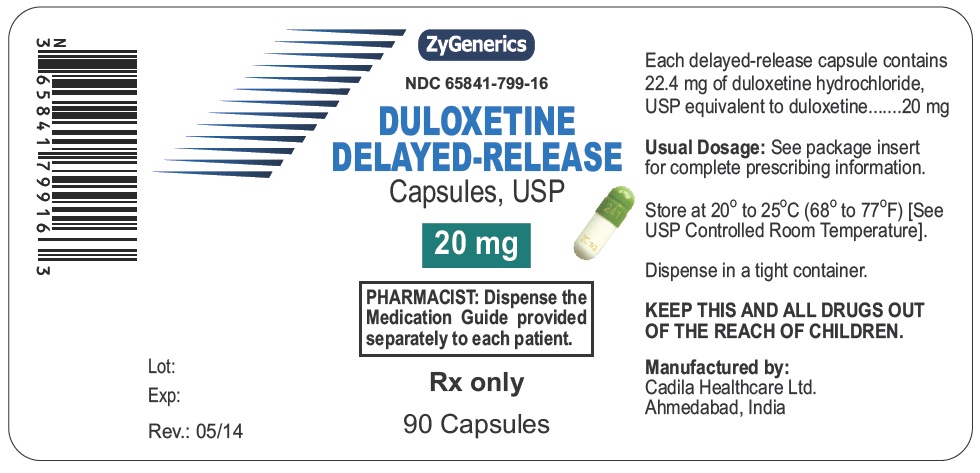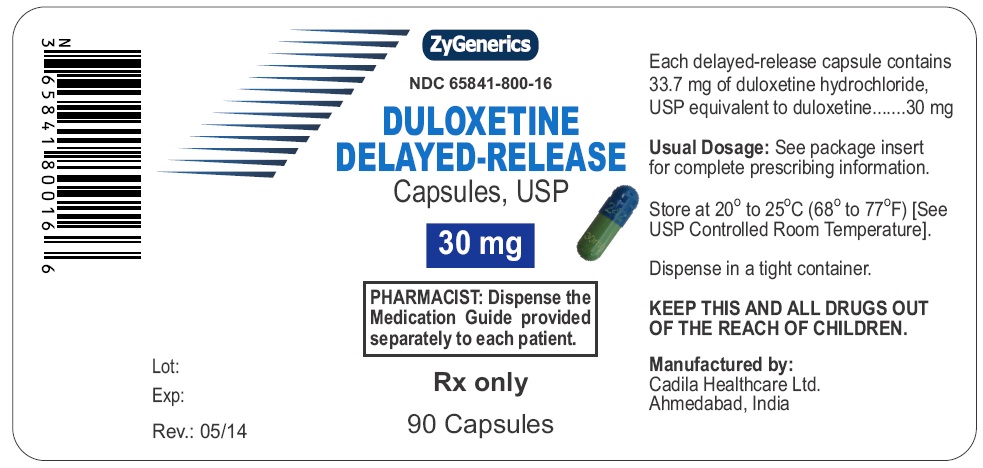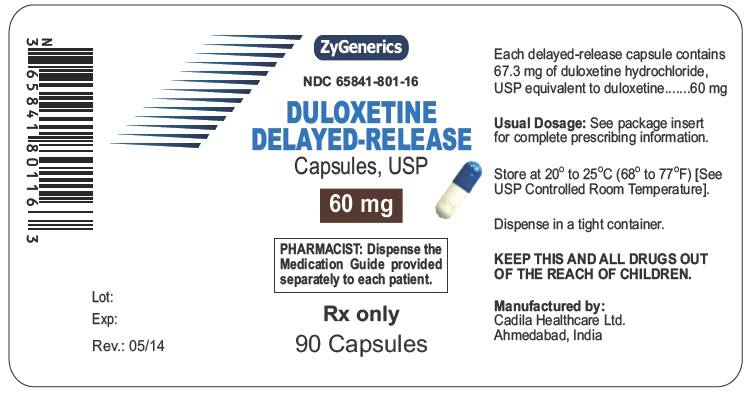 DRUG LABEL: Duloxetine
NDC: 65841-799 | Form: CAPSULE, DELAYED RELEASE
Manufacturer: Zydus Lifesciences Limited
Category: prescription | Type: HUMAN PRESCRIPTION DRUG LABEL
Date: 20241128

ACTIVE INGREDIENTS: DULOXETINE HYDROCHLORIDE 20 mg/1 1
INACTIVE INGREDIENTS: ALCOHOL; AMMONIA; BUTYL ALCOHOL; D&C YELLOW NO. 10; FD&C BLUE NO. 1; FD&C YELLOW NO. 6; FERRIC OXIDE YELLOW; GELATIN; HYPROMELLOSE PHTHALATE (31% PHTHALATE, 40 CST); HYPROMELLOSES; ISOPROPYL ALCOHOL; PROPYLENE GLYCOL; SHELLAC; SODIUM LAURYL SULFATE; STARCH, CORN; SUCROSE; TALC; TITANIUM DIOXIDE; TRIETHYL CITRATE

DULOXETINE DELAYED-RELEASE CAPSULES

MEDICATION GUIDE

Manufactured by:

Cadila Healthcare Ltd.

India

PACKAGE LABEL.PRINCIPAL DISPLAY PANEL

NDC 65841-799-16

Duloxetine Delayed-release Capsules, 20mg

90 Capsules

Rx only

NDC 65841-800-16

Duloxetine Delayed-release Capsules, 30mg

90 Capsules

Rx only

NDC 65841-801-16

Duloxetine Delayed-release Capsules, 60mg

90 Capsules

Rx only